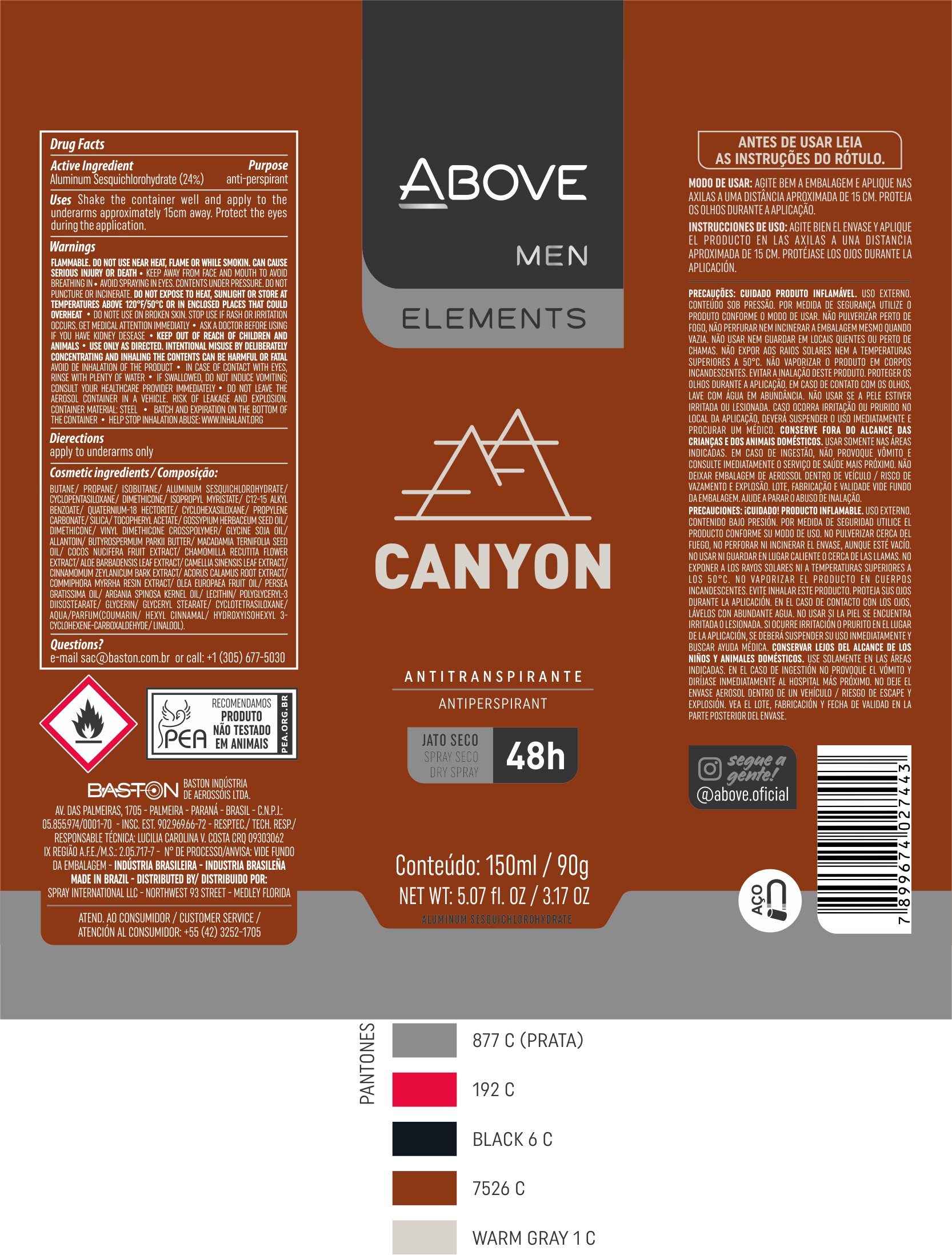 DRUG LABEL: Antiperspirant Above Elements Canyon
NDC: 73306-1115 | Form: AEROSOL, SPRAY
Manufacturer: Baston Industria de Aerossóis Ltda
Category: otc | Type: HUMAN OTC DRUG LABEL
Date: 20241226

ACTIVE INGREDIENTS: ALUMINUM SESQUICHLOROHYDRATE 24 g/100 g
INACTIVE INGREDIENTS: ALLANTOIN; ISOBUTANE; PROPANE; LECITHIN, SOYBEAN; CINNAMON BARK OIL; PROPYLENE CARBONATE; DIMETHICONE; POLYGLYCERYL-3 DIISOSTEARATE; ALOE VERA LEAF; LEVANT COTTON SEED; SILICA DIMETHYL SILYLATE; COCONUT; ACORUS CALAMUS ROOT; BUTANE; CHAMOMILE; GLYCERYL MONOSTEARATE; GLYCERIN; ARGAN OIL; VINYL DIMETHICONE/METHICONE SILSESQUIOXANE CROSSPOLYMER; .ALPHA.-TOCOPHEROL ACETATE; DISTEARDIMONIUM HECTORITE; WATER; ISOPROPYL MYRISTATE; AVOCADO OIL; GREEN TEA LEAF; CYCLOMETHICONE 5; MACADAMIA OIL; SHEA BUTTER; MYRRH OIL

Antiperspirant Above Elements Canyon Aerosol